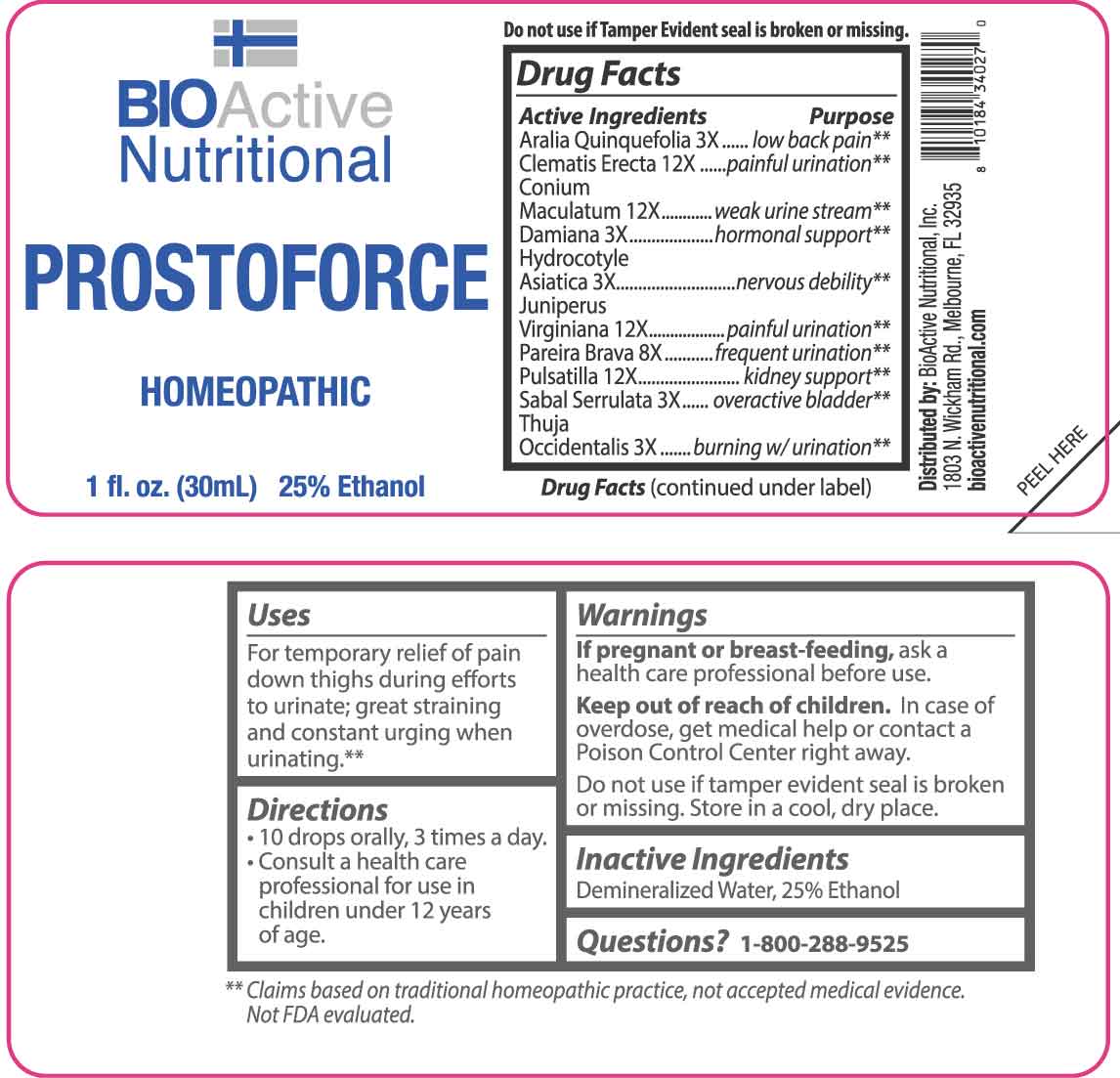 DRUG LABEL: Prostoforce
NDC: 43857-0560 | Form: LIQUID
Manufacturer: BioActive Nutritional, Inc.
Category: homeopathic | Type: HUMAN OTC DRUG LABEL
Date: 20251211

ACTIVE INGREDIENTS: AMERICAN GINSENG 3 [hp_X]/1 mL; TURNERA DIFFUSA LEAFY TWIG 3 [hp_X]/1 mL; CENTELLA ASIATICA WHOLE 3 [hp_X]/1 mL; SAW PALMETTO 3 [hp_X]/1 mL; THUJA OCCIDENTALIS LEAFY TWIG 3 [hp_X]/1 mL; CHONDRODENDRON TOMENTOSUM ROOT 8 [hp_X]/1 mL; CLEMATIS RECTA FLOWERING TOP 12 [hp_X]/1 mL; CONIUM MACULATUM FLOWERING TOP 12 [hp_X]/1 mL; JUNIPERUS VIRGINIANA TWIG 12 [hp_X]/1 mL; PULSATILLA VULGARIS WHOLE 12 [hp_X]/1 mL
INACTIVE INGREDIENTS: WATER; ALCOHOL

DRUG FACTS:

ACTIVE INGREDIENTS:

Aralia Quinquefolia 3X, Clematis Erecta 12X, Conium Maculatum 12X, Damiana 3X, Hydrocotyle Asiatica 3X, Juniperus Virginiana 12X, Pareira Brava 8X, Pulsatilla 12X, Sabal Serrulata 3X, Thuja Occidentalis 3X.

PURPOSE:

Aralia Quinquefolia – low back pain,** Clematis Erecta – painful urination,** Conium Maculatum - weak urine stream,** Damiana – hormonal support,** Hydrocotyle Asiatica – nervous debility,** Juniperus Virginiana – painful urination,** Pareira Brava – frequent urination,** Pulsatilla – kidney support,** Sabal Serrulata – overactive bladder,** Thuja Occidentalis – burning w/urination**

**Claims based on traditional homeopathic practice, not accepted medical evidence. Not FDA evaluated.

USES:

For temporary relief of pain down thighs during efforts to urinate; great straining and constant urging when urinating.**

**Claims based on traditional homeopathic practice, not accepted medical evidence. Not FDA evaluated.

WARNINGS:

If pregnant or breast-feeding, ask a health care professional before use.

Keep out of reach of children. In case of overdose, get medical help or contact a Poison Control Center right away.

Do not use if tamper evident seal is broken or missing.

Store in a cool, dry place.

KEEP OUT OF REACH OF CHILDREN:

In case of overdose, get medical help or contact a Poison Control Center right away.

DIRECTIONS:

• 10 drops orally, 3 times a day.

• Consult a health care professional for use in children under 12 years of age.

INACTIVE INGREDIENTS:

Demineralized Water, 25% Ethanol

QUESTIONS:

Distributed by:
BioActive Nutritional, Inc.
1803 N. Wickham Rd.
Melbourne, FL 32935
bioactivenutritional.com

1-800-288-9525

PACKAGE LABEL DISPLAY:

BIOActive Nutritional

PROSTOFORCE

HOMEOPATHIC

1 fl. oz. (30 mL)